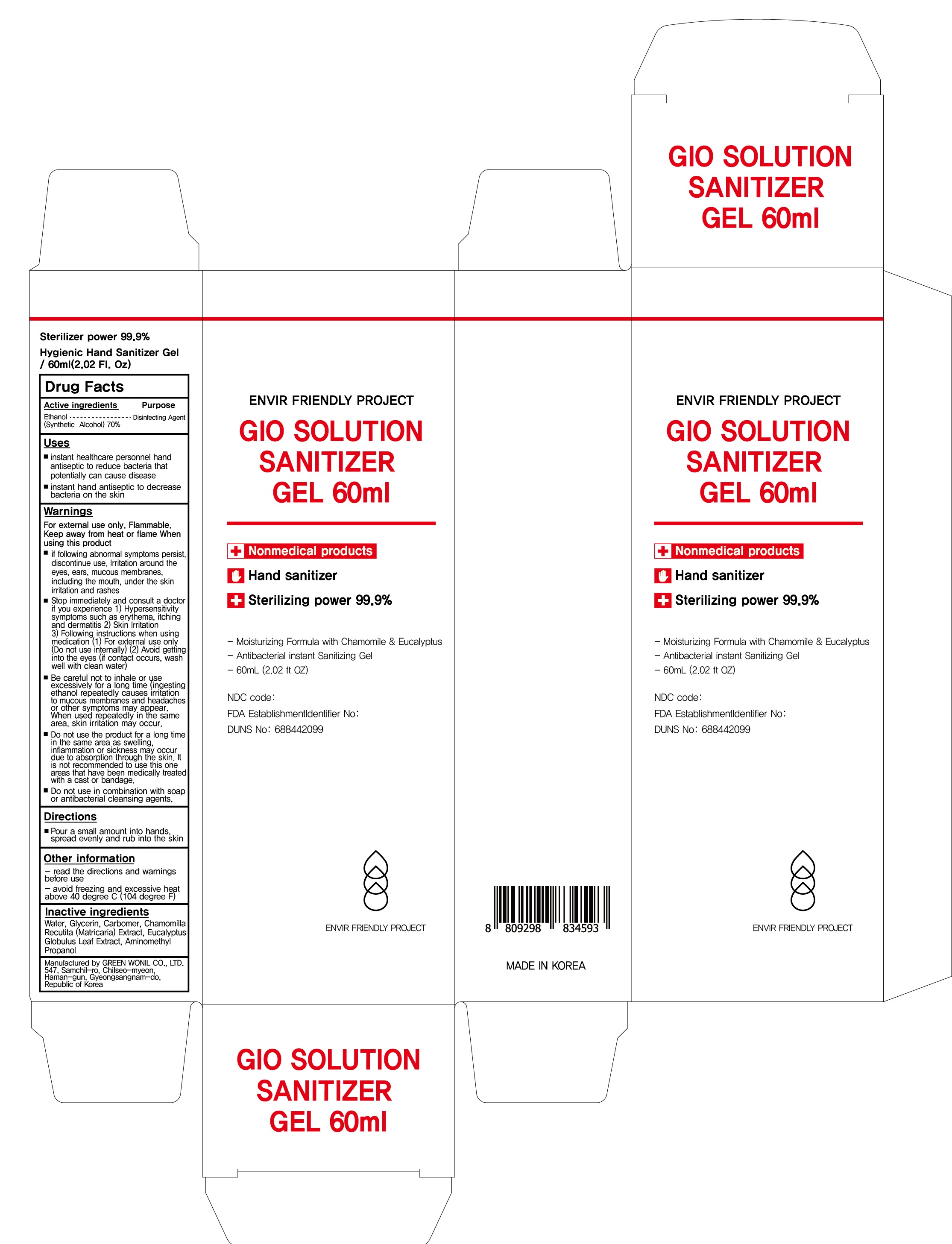 DRUG LABEL: Gio Solution Sanitizer
NDC: 76532-040 | Form: GEL
Manufacturer: GREEN WONIL CO., LTD.
Category: otc | Type: HUMAN OTC DRUG LABEL
Date: 20200602

ACTIVE INGREDIENTS: ALCOHOL 70 mL/100 mL
INACTIVE INGREDIENTS: Water; Glycerin; CARBOMER HOMOPOLYMER, UNSPECIFIED TYPE; MATRICARIA CHAMOMILLA WHOLE; EUCALYPTUS GLOBULUS LEAF; AminomethylPropanol

ACTIVE INGREDIENT

Ethanol (Synthetic Alcohol) 70%

INACTIVE INGREDIENT

Water, Glycerin, Carbomer, Chamomilla Recutita (Matricaria) Extract, Eucalyptus Globulus Leaf Extract, Aminomethyl Propanol

PURPOSE

Disinfecting Agent

WARNINGS

For external use only. Flammable. Keep away from heat or flame

When using this product
if following abnormal symptoms persist, discontinue use. lrritation around the eyes, ears, mucous membranes, including the mouth, under the skin irritation and rashes

Stop immediately and consult a doctor if you experience
1) Hypersensitivity symptoms such as erythema, itching and dermatitis 2) Skin lrritation 3) Following instructions when using medication (1) For external use only (Do not use internally) (2) Avoid getting into the eyes (if contact occurs, wash well with clean water)
Be careful not to inhale or use excessively for a long time (ingesting ethanol repeatedly causes irritation to mucous membranes and headaches or other symptoms may appear. When used repeatedly in the same area, skin irritation may occur.

Do not use the product for a long time in the same area as swelling, inflammation or sickness may occur due to absorption through the skin. It is not recommended to use this one areas that have been medically treated with a cast or bandage.
Do not use in combination with soap or antibacterial cleansing agents.

KEEP OUT OF REACH OF CHILDREN

Uses

• instant healthcare personnel hand antiseptic to reduce bacteria that potentially can cause disease
• instant hand antiseptic to decrease bacteria on the skin

Directions

Pour a small amount into hands, spread evenly and rub into the skin

Other Information

- read the directions and warnings before use
- avoid freezing and excessive heat above 40 degree C (104 degree F)